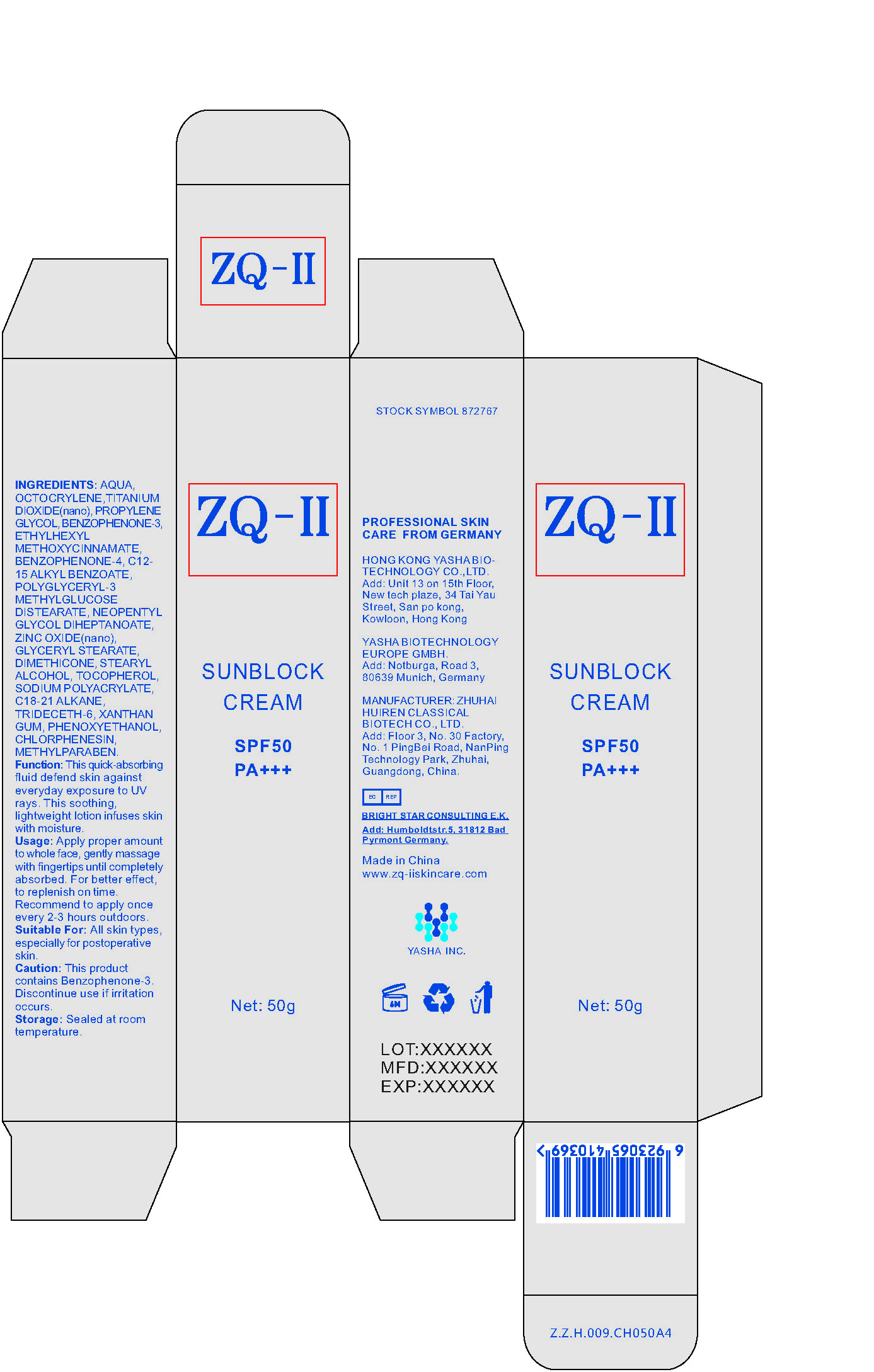 DRUG LABEL: Sunblock Cream
NDC: 80376-001 | Form: CREAM
Manufacturer: Zhuhai Yasha Medical Instrument Co., Ltd.
Category: otc | Type: HUMAN OTC DRUG LABEL
Date: 20200831

ACTIVE INGREDIENTS: OCTISALATE 9 g/100 g; TITANIUM DIOXIDE 6 g/100 g; ZINC OXIDE 3 g/100 g
INACTIVE INGREDIENTS: NEOPENTYL GLYCOL DIHEPTANOATE 3 g/100 g; WATER 45.8 g/100 g; PHENOXYETHANOL 0.2 g/100 g

PACKAGE LABEL

50g in a bottle NDC: 80376-001-01